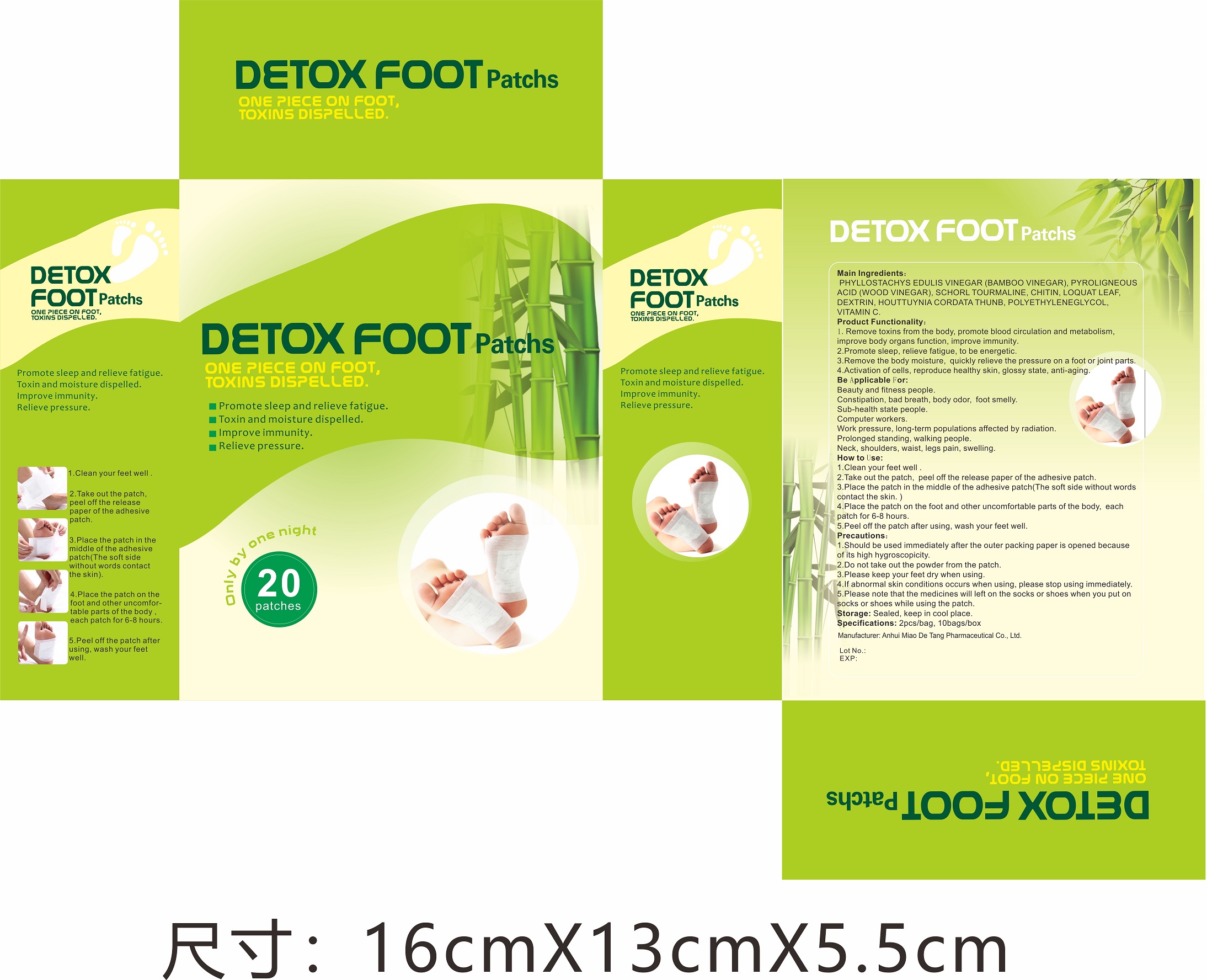 DRUG LABEL: Detox Foot Patch
NDC: 81484-101 | Form: PATCH
Manufacturer: Anhui Miao De Tang Pharmaceutical Co., Ltd.
Category: otc | Type: HUMAN OTC DRUG LABEL
Date: 20230704

ACTIVE INGREDIENTS: HOUTTUYNIA CORDATA WHOLE 0.7875 g/1 1; PYROLIGNEOUS ACID 1.75 g/1 1; SCHORL TOURMALINE 0.2625 g/1 1; PHYLLOSTACHYS EDULIS VINEGAR 2.625 g/1 1
INACTIVE INGREDIENTS: POLYETHYLENE GLYCOL, UNSPECIFIED; ASCORBIC ACID; CHITIN; ERIOBOTRYA JAPONICA LEAF; DEXTRIN PALMITATE (CORN; 20000 MW)

Detox Foot Patch

Detox Foot Patch

Active Ingredient(s)

PHYLLOSTACHYS EDULIS VINEGAR(Bamboo vinegar) 2.625g/patch
Pyroligneous acid(wood vinegar) 1.75g/patch
SCHORL TOURMALINE 0.2625g/patch
Houttuynia cordata thunb 0.7875g/patch

Purpose

Detox Foot Patchs

Use

Detox Foot Patchs to help promote sleep, relieve fatigue.

Warnings

For external use only.

Do not use

- in children less than 12 years of age
- on open skin wounds

Do not use otherwise than directed.Do not stretch out the adhesive tape.Do not take out the contents from the patch.If patch is damaged, discard it right away. Stop use and ask a doctor if irritation or rash occurs. These may be signs of a serious condition.

Keep out of reach of children.

Stop use and ask a doctor if irritation or rash occurs. These may be signs of a serious condition.

Keep out of reach of children.

Directions

Clean your feet well.

Take out the patch, peel off the release paper of the adhesive patch.

Place the patch in the middle of the adhesive patch(The soft side without words contact the skin.)

Plase the patch on the foot and other uncomfortable parts of the body, each patch for 6-8 hours.

Peel off the patch after using, wash your fee well.

Other information

- Sealed, keep in cool place.

Inactive ingredients

Chitin
Loquat leaf
Dextrin
Polyethyleneglycol
Vitamin C